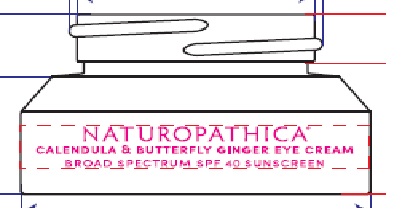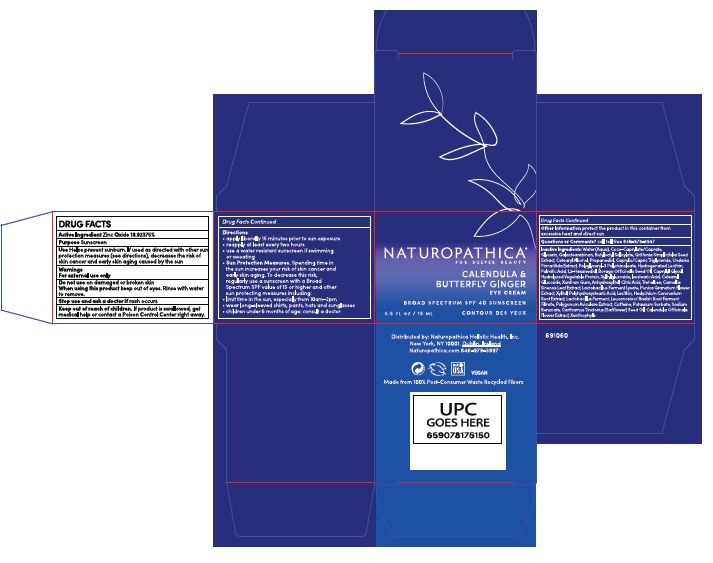 DRUG LABEL: Naturopathica Calendula and Butterfly Ginger
NDC: 54111-153 | Form: CREAM
Manufacturer: Bentley Laboratories, LLC
Category: otc | Type: HUMAN OTC DRUG LABEL
Date: 20210210

ACTIVE INGREDIENTS: ZINC OXIDE 19.92375 g/100 mL
INACTIVE INGREDIENTS: WATER; COCO-CAPRYLATE/CAPRATE; GLYCERIN; GALACTOARABINAN; BUTYLOCTYL SALICYLATE; GRIFFONIA SIMPLICIFOLIA SEED; CETOSTEARYL ALCOHOL; PROPANEDIOL; MEDIUM-CHAIN TRIGLYCERIDES; UNDARIA PINNATIFIDA; POLYGLYCERYL-3 PENTARICINOLEATE; HYDROGENATED SOYBEAN LECITHIN; PALMITIC ACID; 1,2-HEXANEDIOL; BORAGE SEED OIL; CAPRYLYL GLYCOL; XYLITYLGLUCOSIDE; ISOSTEARIC ACID; CETEARYL GLUCOSIDE; XANTHAN GUM; ANHYDROXYLITOL; CITRIC ACID MONOHYDRATE; TREHALOSE; GREEN TEA LEAF; PUNICA GRANATUM FLOWER; XYLITOL; POLYHYDROXYSTEARIC ACID (2300 MW); LECITHIN, SOYBEAN; HEDYCHIUM CORONARIUM ROOT; LEUCONOSTOC/RADISH ROOT FERMENT FILTRATE; POLYGONUM AVICULARE TOP; CAFFEINE; POTASSIUM SORBATE; SODIUM BENZOATE; SAFFLOWER OIL; CALENDULA OFFICINALIS FLOWER; LUTEIN

NATUROPATHICA CALENDULA & BUTTERFLY GINGER EYE CREAM

Drug Facts

Active Ingredient

Zinc Oxide 19.92375%

Purpose

Sunscreen

Uses

Helps prevent sunburn. If used as directed with

other sun protection measures (see directions),

decreases the risk of skin cancer and early skin

aging caused by the sun

Warnings

For external use only
Do not use on damaged or broken skin
When using this product keep out of eyes.
Rinse with water to remove.
Stop use and ask a doctor if rash occurs

Keep out of reach of children. If product is

swallowed, get medical help or contact a Poison

Control Center right away.

Directions

• apply liberally 15 minutes before sun exposure
• reapply at least every two hours
• use a water resistant sunscreen if swimming or sweating
• Sun Protection Measures. Spending time in
the sun increases your risk of skin cancer and
early skin aging. To decrease this risk,
regularly use a sunscreen with a Broad
Spectrum SPF 15 or higher and other
sun protection measures including:
• limit time in the sun, especially from 10a.m. - 2p.m.
• wear long-sleeved shirts, pants, hats and sunglasses
• children under 6 months of age: consult a doctor

Other Information

Protect the product in this container from excessive heat and direct sun

Questions or Comments? call toll free 646-979-3997

Inactive Ingredients: Water (Aqua), Coco-Caprylate/Caprate,
Glycerin, Galactoarabinan, Butyloctyl Salicylate, Griffonia Simplicifolia Seed
Extract, Cetearyl Alcohol, Propanediol, Caprylic/Capric Triglyceride, Undaria
Pinnatifida Extract, Polyglyceryl-3 Polyricinoleate, Hydrogenated Lecithin,
Palmitic Acid, 1,2-Hexanediol, Borago Officinalis Seed Oil, Caprylyl Glycol,
Hydrolyzed Vegetable Protein, Xylitylglucoside, Isostearic Acid, Cetearyl
Glucoside, Xanthan Gum, Anhydroxylitol, Citric Acid, Trehalose, Camellia
Sinensis Leaf Extract, Lactobacillus Ferment Lysate, Punica Granatum Flower
Extract, Xylitol, Polyhydroxystearic Acid, Lecithin, Hedychium Coronarium
Root Extract, Lactobacillus Ferment, Leuconostoc/Radish Root Ferment
Filtrate, Polygonum Aviculare Extract, Caffeine, Potassium Sorbate, Sodium
Benzoate, Carthamus Tinctorius (Safflower) Seed Oil, Calendula Officinalis
Flower Extract, Xanthophylls

Product Label

NATUROPATHICA®

FOR DEEPER BEAUTY

CALENDULA &

BUTTERFLY GINGER

EYE CREAM

BROAD SPECTRUM SPF 40 SUNSCREEN

FLUIDE ESSENTIAL

HYDRATANT

0.5 FL OZ/50 ML

Distributed by: Naturopathica Holistic Health, Inc.

New York, NY 10001. Dublin, Ireland

Naturopathica.com 646-979-3997

res